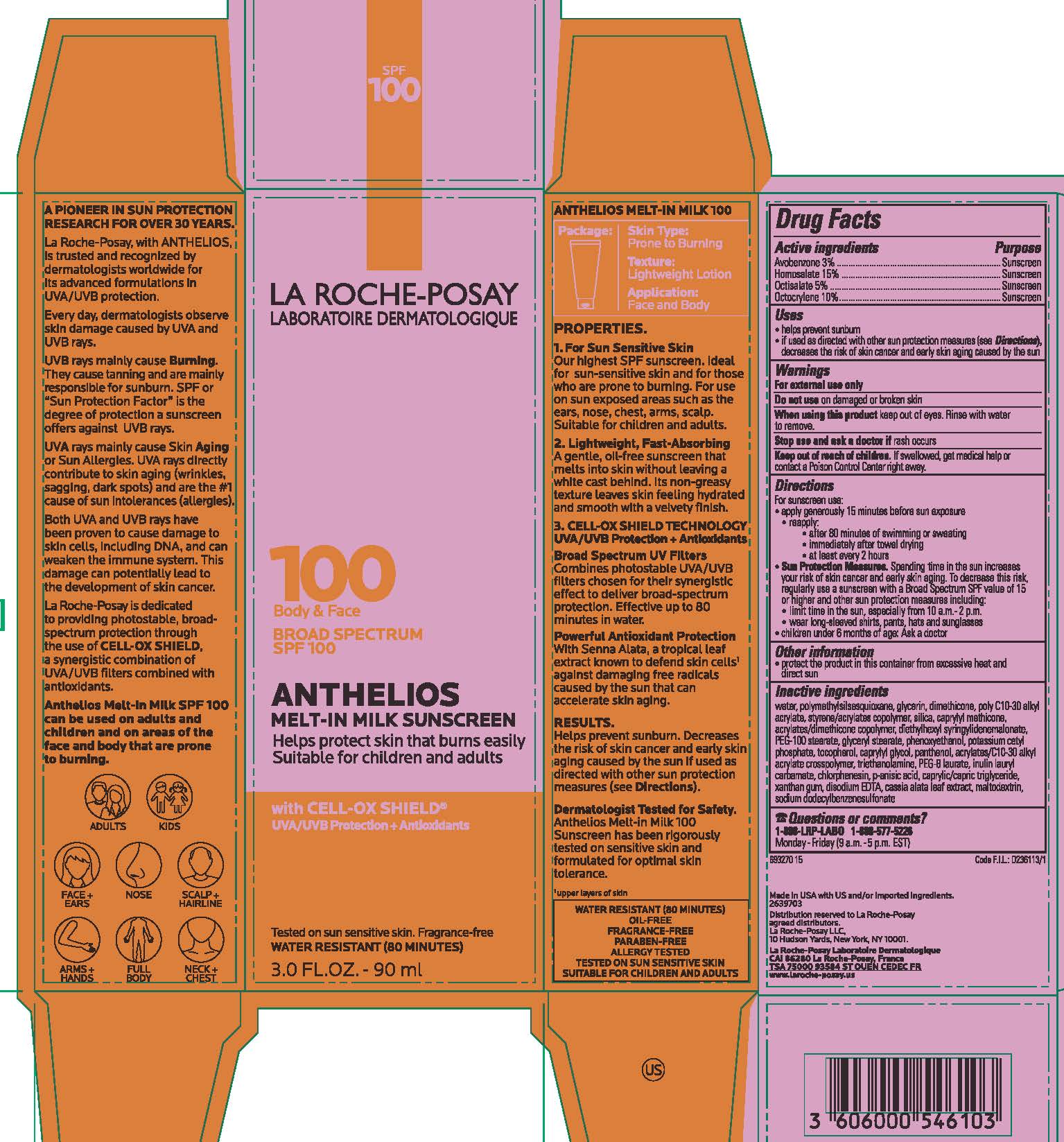 DRUG LABEL: La Roche Posay Laboratoire Dermatologique Anthelios Broad Spectrum SPF 100 Body and Face Melt In Milk Sunscreen Water Resistant 80 Minutes
NDC: 49967-103 | Form: LOTION
Manufacturer: L'Oreal USA Products Inc
Category: otc | Type: HUMAN OTC DRUG LABEL
Date: 20231228

ACTIVE INGREDIENTS: AVOBENZONE 30 mg/1 mL; HOMOSALATE 150 mg/1 mL; OCTISALATE 50 mg/1 mL; OCTOCRYLENE 10 mg/1 mL
INACTIVE INGREDIENTS: WATER; POLYMETHYLSILSESQUIOXANE (4.5 MICRONS); GLYCERIN; DIMETHICONE; STYRENE/ACRYLAMIDE COPOLYMER (500000 MW); SILICON DIOXIDE; CAPRYLYL TRISILOXANE; DIETHYLHEXYL SYRINGYLIDENEMALONATE; PEG-100 STEARATE; GLYCERYL MONOSTEARATE; PHENOXYETHANOL; POTASSIUM CETYL PHOSPHATE; TOCOPHEROL; CAPRYLYL GLYCOL; PANTHENOL; CARBOMER INTERPOLYMER TYPE A (ALLYL SUCROSE CROSSLINKED); TROLAMINE; PEG-8 LAURATE; CHLORPHENESIN; P-ANISIC ACID; MEDIUM-CHAIN TRIGLYCERIDES; XANTHAN GUM; EDETATE DISODIUM; SENNA ALATA LEAF; MALTODEXTRIN; SODIUM DODECYLBENZENESULFONATE

Drug Facts

Active ingredients

Avobenzone 3%

Homosalate 15%

Octisalate 5%

Octocrylene 10%

Purpose

Sunscreen

Uses

- helps prevent sunburn

- if used as directed with other sun protection measures (see Directions), decreases the risk of skin cancer and early skin aging caused by the sun

Warnings

For external use only

Do not use

on damaged or broken skin

When using this product

keep out of eyes. Rinse with water to remove.

Stop use and ask a doctor if

rash occurs

Keep out of reach of children.

If swallowed, get medical help or contact a Poison Control Center right away.

Directions

For sunscreen use:

● apply generously 15 minutes before sun exposure

● reapply:

● after 80 minutes of swimming or sweating

● immediately after towel drying

● at least every 2 hours

● Sun Protection Measures. Spending time in the sun increases your risk of skin cancer and early skin aging. To decrease this risk, regularly use a sunscreen with a Broad Spectrum SPF value of 15 or higher and other sun protection measures including:

● limit time in the sun, especially from 10 a.m. – 2 p.m.

● wear long-sleeved shirts, pants, hats, and sunglasses

● children under 6 months of age: Ask a doctor

Other information

protect the product in this container from excessive heat and direct sun

Inactive ingredients

water, polymethylsilsesquioxane, glycerin, dimethicone, poly c10-30 alkyl acrylate, styrene/acrylates copolymer, silica, caprylyl methicone, acrylates/dimethicone copolymer, diethylhexyl syringylidenemalonate, PEG-100 stearate, glyceryl stearate, phenoxyethanol, potassium cetyl phosphate, tocopherol, caprylyl glycol, panthenol, acrylates/c10-30 alkyl acrylate crosspolymer, triethanolamine, PEG-8 laurate, inulin lauryl carbamate, chlorphenesin, p-anisic acid, caprylic/capric triglyceride, xanthan gum, disodium EDTA, cassia alata leaf extract, maltodextrine, sodium dodecylbenzenesulfonate

Questions or comments?

1-888-LRP-LAB0 1-888-577-5226

Monday - Friday (9 a.m. - 5 p.m. EST)